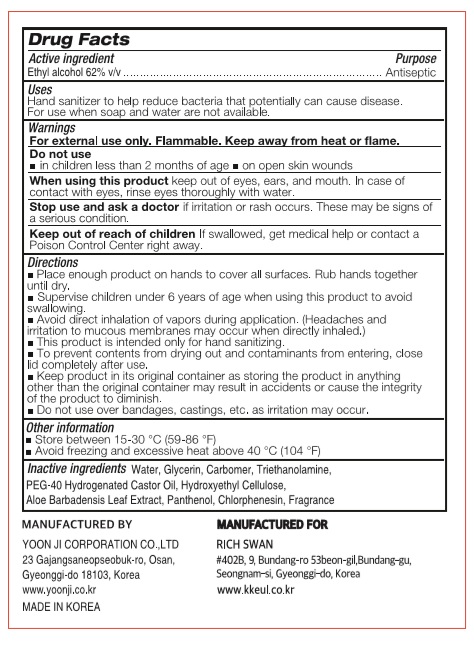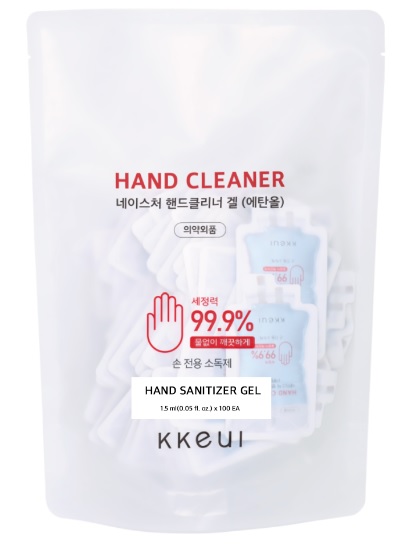 DRUG LABEL: HAND CLEANER
NDC: 75024-150 | Form: GEL
Manufacturer: YOON JI CORPORATION CO.,LTD
Category: otc | Type: HUMAN OTC DRUG LABEL
Date: 20200521

ACTIVE INGREDIENTS: ALCOHOL 0.93 mL/1.5 mL
INACTIVE INGREDIENTS: POLYOXYL 40 HYDROGENATED CASTOR OIL; ALOE VERA LEAF; GLYCERIN; CARBOMER HOMOPOLYMER, UNSPECIFIED TYPE; WATER; PANTHENOL; CHLORPHENESIN; HYDROXYETHYL CELLULOSE, UNSPECIFIED; TROLAMINE

[RICH SWAN] HAND CLEANER 75024-150-10